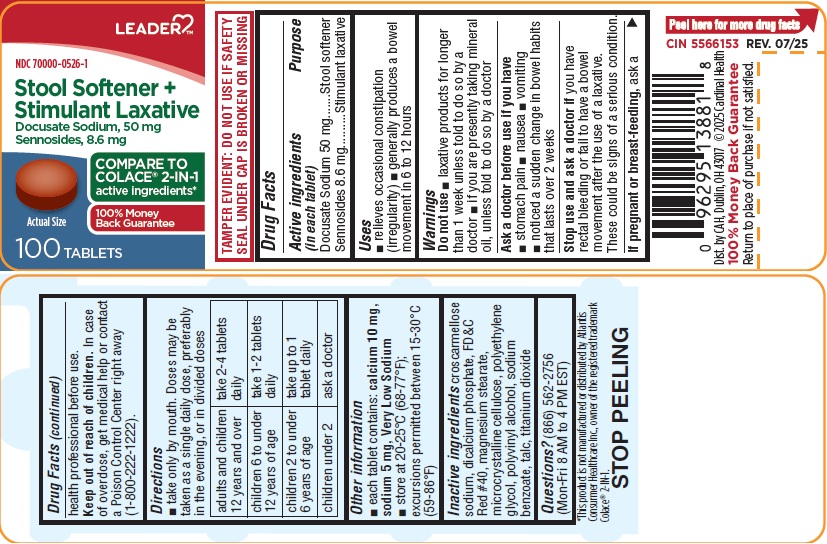 DRUG LABEL: Stool Softener plus Stimulant Laxative
NDC: 70000-0526 | Form: TABLET, FILM COATED
Manufacturer: CARDINAL HEALTH, 110 DBA LEADER
Category: otc | Type: HUMAN OTC DRUG LABEL
Date: 20251223

ACTIVE INGREDIENTS: SENNOSIDES 8.6 mg/1 1; DOCUSATE SODIUM 50 mg/1 1
INACTIVE INGREDIENTS: CROSCARMELLOSE SODIUM; CALCIUM PHOSPHATE, DIBASIC, DIHYDRATE; FD&C RED NO. 40; MAGNESIUM STEARATE; CELLULOSE, MICROCRYSTALLINE; POLYETHYLENE GLYCOL, UNSPECIFIED; POLYVINYL ALCOHOL, UNSPECIFIED; SODIUM BENZOATE; TALC; TITANIUM DIOXIDE

Drug Facts

Active Ingredients (in each tablet)

Docusate Sodium 50 mg

Sennosides 8.6 mg

Purpose

Stool softener

Stimulant laxative

Uses

- relieves occasional constipation (irregularity)
- generally produces a bowel movement in 6 to 12 hours

Warnings

Do not use

- laxative products for longer than 1 week unless told to do so by a doctor
- if you are presently taking mineral oil, unless told to do so by a doctor

Ask a doctor before use if you have

- stomach pain
- nausea
- vomiting
- noticed a sudden change in bowel habits that lasts over 2 weeks

Stop use and ask a doctor if

you have rectal bleeding or fail to have a bowel movement after the use of a laxative.

These could be sings of a serious condition.

If pregnant or breast-feeding,

ask a health professional before use.

Keep out of reach of children.

In case of overdose, get medical help or contact a Poison Control Center right away (1-800-222-1222).

Directions

- take only by mouth. Doses may be taken as a single daily dose, preferably in the evening, or in divided doses

adults and children 12 years and over | take 2-4 tablets daily
children 6 to under 12 years of age | take 1-2 tablets daily
children 2 to under 6 years of age | take upto 1 tablet daily
children under 2 | ask a doctor

Other information

- each tablet contains: calcium 10 mg, sodium 5 mg, Very Low Sodium
- store at 20-25°C (68-77°F); excursions permitted between 15-30oC (59-86oF)

Inactive ingredients

croscarmellose sodium, dicalcium phosphate, FD&C Red #40, magnesium stearate, microcrystalline cellulose, polyethylene glycol, polyvinyl alcohol, sodium benzoate, talc, titanium dioxide

Questions?

(866) 562-2756 (Mon-Fri 8 AM to 4 PM EST)

PACKAGE LABEL

LEADER TM

NDC 70000-0526-1

Stool Softener +

Stimulant Laxative

Docusate Sodium, 50 mg

Sennosides, 8.6 mg

COMPARE TO

COLACE® 2-IN-1

active ingredients*

100% Money

Back Guarantee

100 TABLETS